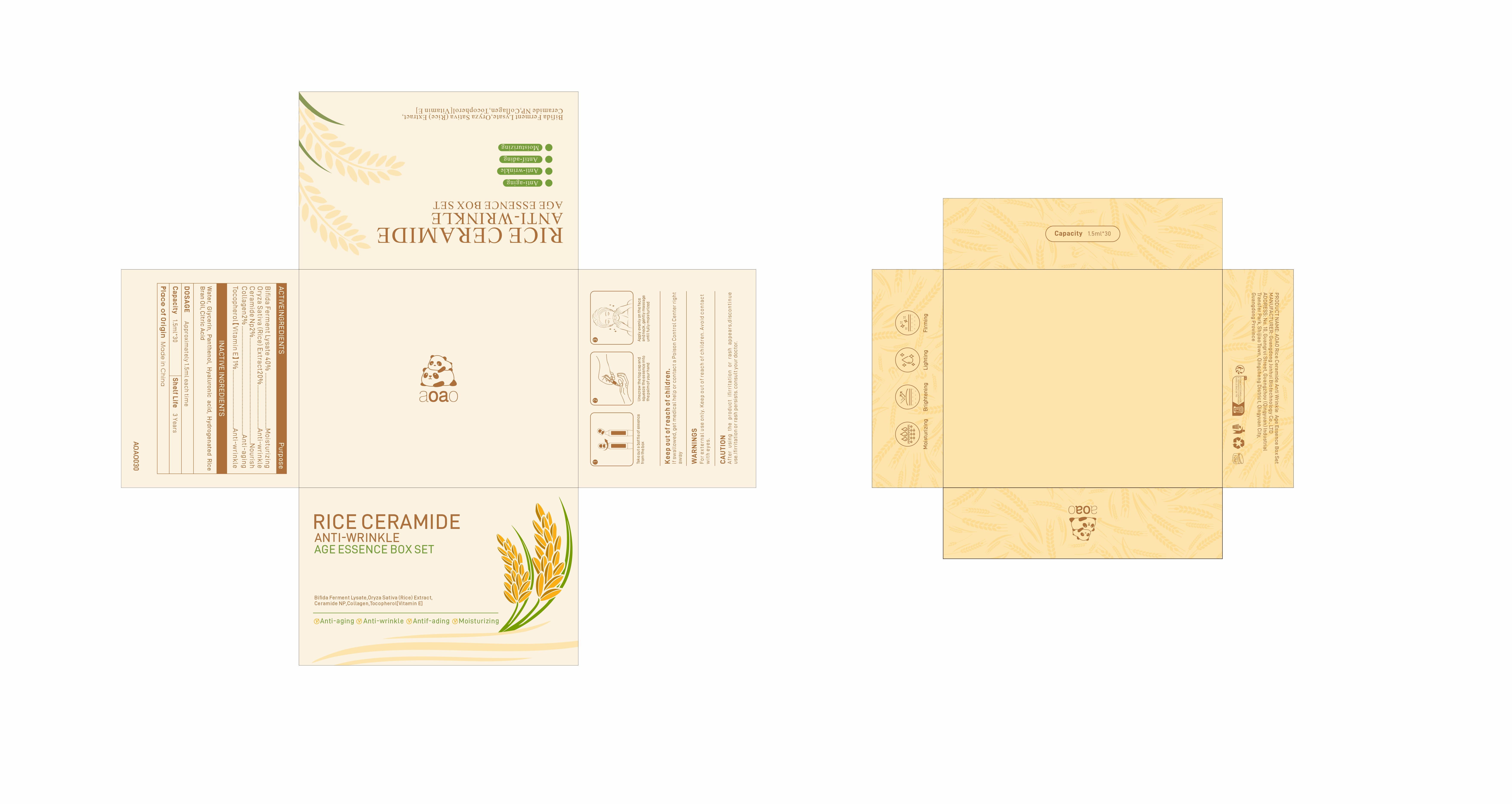 DRUG LABEL: AOAO Rice Ceramide Anti Wrinkle Age Essence Box Set
NDC: 84509-037 | Form: LIQUID
Manufacturer: Guangdong Junhui Biotechnology Co., LTD
Category: otc | Type: HUMAN OTC DRUG LABEL
Date: 20241029

ACTIVE INGREDIENTS: YEAST EXTRACT 600 mg/1.5 mL; CERAMIDE NP 30 mg/1.5 mL; RICE GERM 300 mg/1.5 mL; COLLAGEN, SOLUBLE, FISH SKIN 30 mg/1.5 mL; TOCOPHEROL 15 mg/1.5 mL
INACTIVE INGREDIENTS: HYALURONIC ACID; PANTHENOL; WATER; GLYCERIN; TRIBUTYL CITRATE; RICE BRAN OIL

Active Ingredients

Bifida Ferment Lysate 40%
Oryza Sativa (Rice) Extract 20%
Ceramide NP 2%
Collagen 2%
Tocopherol【Vitamin E】 1%

Purpose

Moisturizing
Anti-wrinkle
Nourish
Anti-aging

Uses

1. Take out a bottle of essence from the box
2. Unscrew the top cap and squeeze the essence into the palm of your hand
3. Apply evenly on the face and neck, gently massage until fully moisturized

DOSAGE

Approximately 0.15ml each time

Warnings

For external use only. Keep out ofreach of children.Avoid contact with eyes.

Keep out of reach of children

If swallowed, get medical help or contact a Poison Control Center right away

CAUTION

After using the product if irritation or rash appears,discontinue use.If irritation or rash persists.consult your doctor.

Inactive Ingredients

Water,Glycerin，Panthenol,Hyaluronic acid,Hydrogenated Rice Bran Oil，Citric Acid

Product Name

AOAO Rice Ceramide Anti Wrinkle Age Essence Box Set

Address

No. 10, Guangrui Street, Guangzhou (Qingyuan) Industrial Transfer Park, Shijiao Town, Qingcheng District, Qingyuan City, Guangdong Province

MANUFACTURER

Guangdong Junhui Biotechnology Co., LTD

Capacity

1.5ml*30

Shelf Life

3 Years

Place of Origin

Made in China